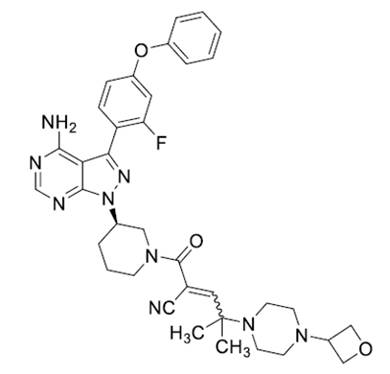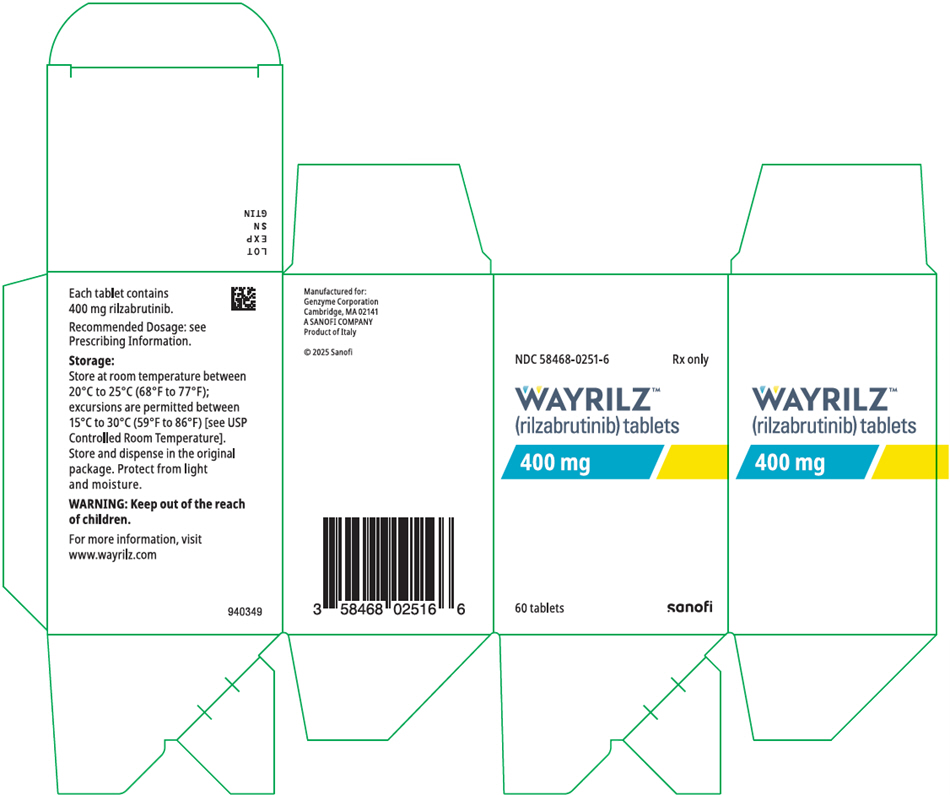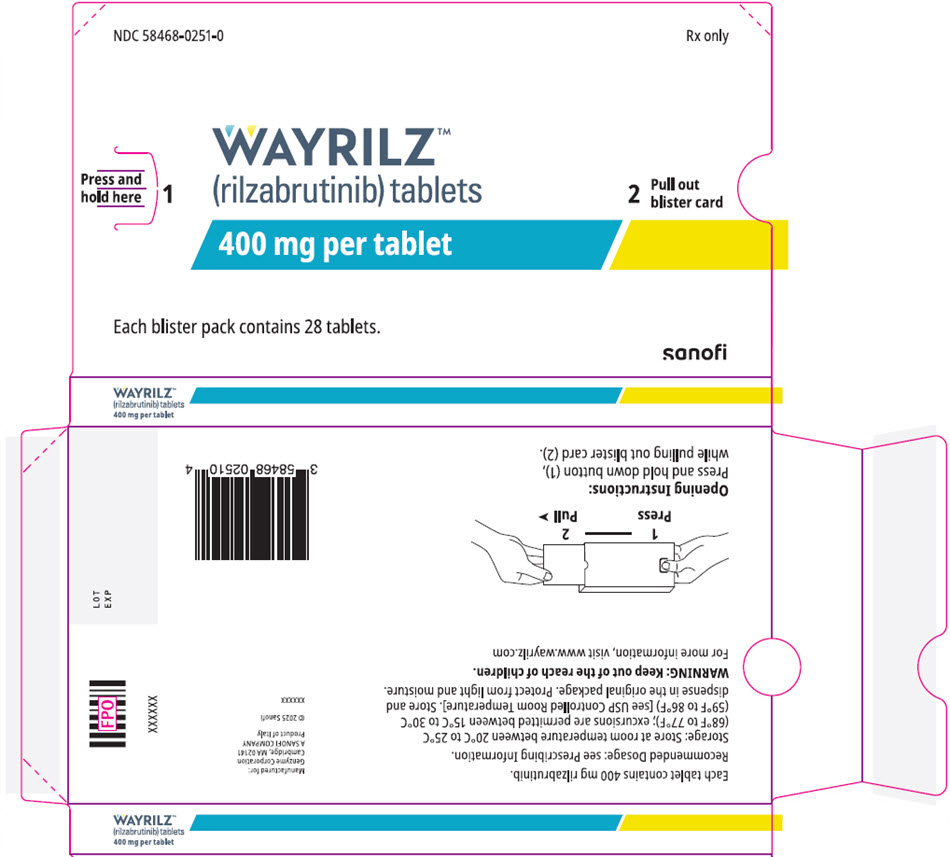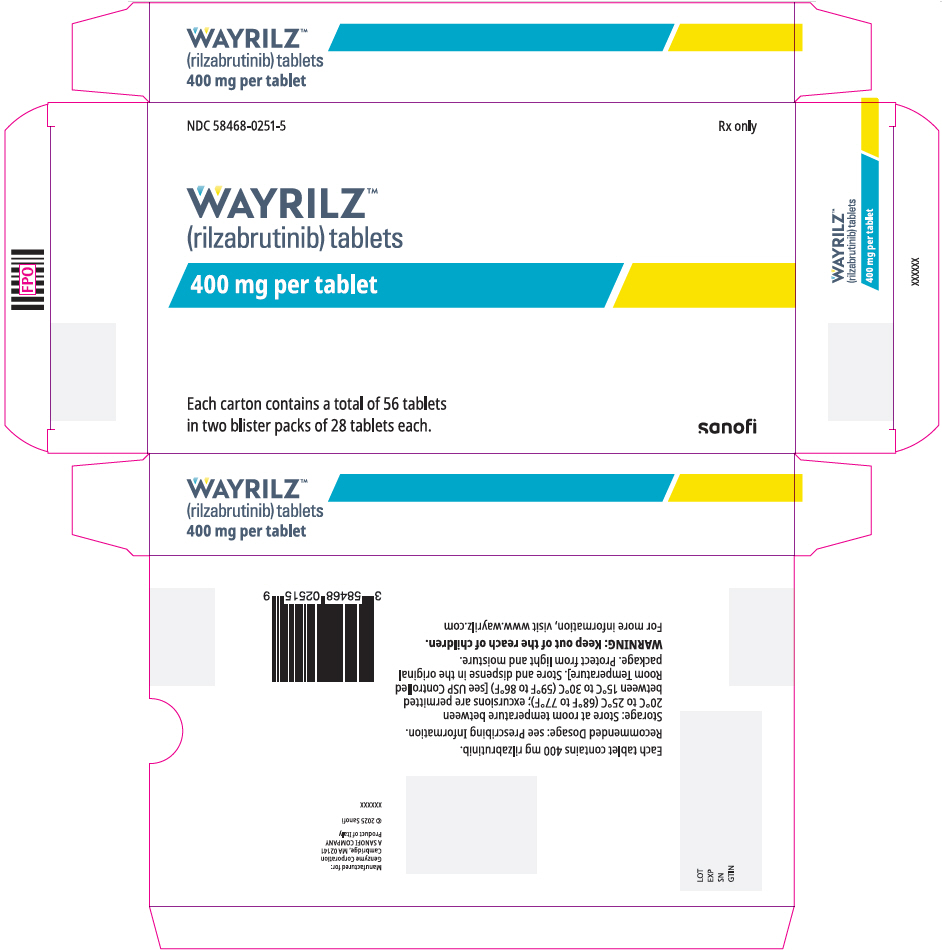 DRUG LABEL: WAYRILZ
NDC: 58468-0251 | Form: TABLET, FILM COATED
Manufacturer: Genzyme Corporation
Category: prescription | Type: HUMAN PRESCRIPTION DRUG LABEL
Date: 20250826

ACTIVE INGREDIENTS: RILZABRUTINIB 400 mg/1 1
INACTIVE INGREDIENTS: CROSPOVIDONE, UNSPECIFIED; MICROCRYSTALLINE CELLULOSE; POLYVINYL ALCOHOL, UNSPECIFIED; TITANIUM DIOXIDE; POLYETHYLENE GLYCOL, UNSPECIFIED; TALC; FD&C YELLOW NO. 6; SODIUM STEARYL FUMARATE

HIGHLIGHTS OF PRESCRIBING INFORMATION

These highlights do not include all the information needed to use WAYRILZ™ safely and effectively. See full prescribing information for WAYRILZ.
WAYRILZ™ (rilzabrutinib) tablets, for oral use
Initial U.S. Approval: 2025

1 INDICATIONS AND USAGE

WAYRILZ is a kinase inhibitor indicated for the treatment of adult patients with persistent or chronic immune thrombocytopenia (ITP) who have had an insufficient response to a previous treatment. (1)

2 DOSAGE AND ADMINISTRATION

- See Full Prescribing Information for important recommendations prior to treatment. (2.1, 2.3)
- Recommended dosage: 400 mg orally twice daily; swallow whole with water, with or without food. Do not cut, crush, or chew tablets. (2.2)

3 DOSAGE FORMS AND STRENGTHS

Tablets: 400 mg (3)

4 CONTRAINDICATIONS

None

5 WARNINGS AND PRECAUTIONS

- Serious Infections: Monitor patients for signs and symptoms of infection, evaluate promptly, and treat. (5.1)
- Hepatotoxicity, Including Drug-Induced Liver Injury: Evaluate bilirubin and transaminases at baseline and as clinically indicated during treatment. (5.2)
- Embryo-Fetal Toxicity: Based on preliminary animal data, WAYRILZ may cause fetal harm. Advise females of reproductive potential of the potential risk and to use effective contraception. (5.3, 8.1, 8.3)

6 ADVERSE REACTIONS

Most common adverse reactions (incidence ≥10%) were diarrhea, nausea, headache, abdominal pain, and COVID-19. (6.1)

To report SUSPECTED ADVERSE REACTIONS, contact Genzyme Corporation at 1-800-633-1610 or FDA at 1-800-FDA-1088 or www.fda.gov/medwatch.

7 DRUG INTERACTIONS

- CYP3A Inhibitors: Avoid co-administration with moderate or strong CYP3A inhibitors. (7.1)
- CYP3A Inducers: Avoid co-administration with moderate or strong CYP3A inducers. (7.1)
- Gastric Acid Reducing Agents: Avoid co-administration with proton pump inhibitors (PPIs). WAYRILZ should be administered at least 2 hours before taking an antacid or H2 receptor antagonist. (7.1)

8 USE IN SPECIFIC POPULATIONS

- Lactation: Advise not to breastfeed. (8.2)
- Hepatic Impairment: Avoid use of WAYRILZ in patients with moderate or severe hepatic impairment. (8.6)
- Renal Impairment: Avoid use in patients with severe renal impairment. (8.7)

FULL PRESCRIBING INFORMATION

1 INDICATIONS AND USAGE

WAYRILZ is indicated for the treatment of adult patients with persistent or chronic immune thrombocytopenia (ITP) who have had an insufficient response to a previous treatment.

2 DOSAGE AND ADMINISTRATION

2.1 Recommended Testing Before Initiating WAYRILZ

Verify pregnancy status of females of reproductive potential prior to initiating WAYRILZ treatment [see Warnings and Precautions (5.3) and Use in Specific Populations (8.1, 8.3)].

2.2 Recommended Dosage

The recommended dosage of WAYRILZ is 400 mg taken orally twice daily.

WAYRILZ can be taken at approximately the same time each day with or without food. In patients who experience gastrointestinal symptoms, taking WAYRILZ with food may improve tolerability. Advise patients to swallow tablets whole with a glass of water. Advise patients not to cut, crush or chew the tablets.

If a dose is missed, patients should take the missed dose of WAYRILZ as soon as possible on the same day and at least 2 hours apart from the next regular scheduled dose.

If taking antacid or histamine H2 receptor antagonist, administer the dose of WAYRILZ at least 2 hours before the antacid or histamine H2 receptor antagonist.

2.3 Monitoring and Dose Modifications for Hepatotoxicity

Evaluate bilirubin and transaminases at baseline and as clinically indicated during treatment with WAYRILZ. For patients who develop abnormal liver tests after WAYRILZ, monitor more frequently for liver test abnormalities and clinical signs and symptoms of hepatic toxicity. If Drug-Induced Liver Injury (DILI) is suspected, withhold WAYRILZ. Upon confirmation of DILI, discontinue WAYRILZ.

3 DOSAGE FORMS AND STRENGTHS

Tablets: Each 400 mg film-coated tablet is orange, capsule-shaped, and debossed with "P" on one side and "400" on the other side.

4 CONTRAINDICATIONS

None

5 WARNINGS AND PRECAUTIONS

5.1 Serious Infections

An increased risk of serious infections (including bacterial, viral, or fungal) can occur in patients treated with Bruton's tyrosine kinase (BTK) inhibitors, including WAYRILZ. In the LUNA-3 trial, fatal pneumonia occurred in one participant in the WAYRILZ group. Other serious infections [one each (0.8%)] included COVID-19 infection, wound infection, and one patient experienced urinary tract infection and kidney abscess. Monitor patients for signs and symptoms of infection and treat appropriately.

5.2 Hepatotoxicity, Including Drug-Induced Liver Injury

Hepatotoxicity, including severe, life-threatening, and potentially fatal cases of DILI, can occur in patients treated with BTK inhibitors. In the clinical trials of WAYRILZ in patients with ITP, elevations of liver transaminases occurred and were generally mild to moderate in severity. Evaluate bilirubin and transaminases at baseline and as clinically indicated during treatment with WAYRILZ. For patients who develop abnormal liver tests after WAYRILZ, monitor more frequently for liver test abnormalities and clinical signs and symptoms of hepatic toxicity. If DILI is suspected, withhold WAYRILZ. Upon confirmation of DILI, discontinue WAYRILZ.

5.3 Embryo-Fetal Toxicity

Based on findings from preliminary animal reproduction studies, WAYRILZ may cause fetal harm when administered to a pregnant woman. Adverse visceral and skeletal findings occurred in rat fetuses at a maternally toxic dose at exposures 22-times the human exposure [based on area under the curve (AUC)] at the maximum recommended human dose (MRHD), and renal visceral malformations occurred in a single rabbit fetus at 5.6-times the human exposure (based on AUC) at the MRHD. Verify pregnancy status of females of reproductive potential prior to initiating WAYRILZ treatment. Advise females of reproductive potential to use an effective method of contraception during treatment with WAYRILZ and for 1 week after the final dose [see Use in Specific Populations (8.1, 8.3)].

6 ADVERSE REACTIONS

The following clinically important adverse reactions are described elsewhere in the labeling:

- Serious Infections [see Warnings and Precautions (5.1)]
- Hepatotoxicity, Including Drug-Induced Liver Injury [see Warnings and Precautions (5.2)]

6.1 Clinical Trials Experience

Because clinical trials are conducted under widely varying conditions, adverse reaction rates observed in the clinical trials of a drug cannot be directly compared to rates in the clinical trials of another drug and may not reflect the rates observed in practice.

The safety of WAYRILZ was evaluated in a randomized, double-blind (DB), placebo-controlled, parallel-group study (LUNA-3), in which 202 adult patients with persistent or chronic ITP received either WAYRILZ (n=133) or placebo (n=69) [see Clinical Studies (14)].

During the 24-week DB period, the median duration of WAYRILZ exposure was 98 days (range: 22 to 182).

The most common adverse reactions (≥10%) were diarrhea, nausea, headache, abdominal pain, and COVID-19. Adverse reactions resulting in discontinuation of WAYRILZ included erythema nodosum, neutropenia, arthralgia, dyspepsia, headache, pain in extremity, abdominal discomfort, diarrhea, nausea, and pneumonia and occurred in 4.5% of patients.

Table 1 presents common adverse reactions from the LUNA-3 Study.

Table 1: Common Adverse Reactions [Adverse reactions that occurred in at least 5% of WAYRILZ treated patients and at least 3% higher than placebo-treated patients.] in Patients with ITP During Double-Blind Period of the LUNA-3 Study
Adverse Reactions | WAYRILZ (N=133) |  | Placebo (N=69)
 | All Grades % | Grade 3 or Higher % | All Grades % | Grade 3 or Higher %
Diarrhea | 32 | 0 | 10 | 0
Nausea | 20 | 0 | 6 | 0
Headache | 18 | 0 | 7 | 0
Abdominal Pain [Grouped term] | 14 | 0 | 1 | 0
COVID-19 | 14 | 0.8 | 4 | 0
Arthralgia | 9 | 0 | 4 | 0
Dizziness | 8 | 0 | 1 | 0
Nasopharyngitis | 7 | 0 | 3 | 0
Vomiting | 7 | 0 | 1 | 0
Dyspepsia | 5 | 0 | 0 | 0
Cough | 5 | 0 | 0 | 0

Specific Adverse Reactions

Gastrointestinal Events

In the LUNA-3 Study DB period, the most common gastrointestinal (GI) adverse reactions were diarrhea (32%), nausea (20%), and abdominal pain (14%) in the WAYRILZ group. These events were Grade 1 or 2. Of those who experienced GI adverse reactions, 2 patients discontinued due to GI adverse reactions. Recovery or resolution with supportive treatment allowing continuation of WAYRILZ treatment occurred in 91% of patients with diarrhea, 85% with nausea and 79% with abdominal pain.

Neutropenia

In the LUNA-3 Study DB period, Grade 1 or 2 neutropenia occurred in 11% of patients in the WAYRILZ group.

7 DRUG INTERACTIONS

7.1 Effect of Other Drugs on WAYRILZ

Strong and Moderate CYP3A Inhibitors

Avoid concomitant use of WAYRILZ with strong or moderate CYP3A inhibitors. If a strong or moderate CYP3A inhibitor cannot be avoided, and these inhibitors will be used short term (such as anti-infectives for seven days or less), interrupt treatment with WAYRILZ. Avoid concomitant use of grapefruit, starfruit and products containing these fruits, and Seville oranges with WAYRILZ, as these are moderate and strong inhibitors of CYP3A.

Rilzabrutinib is a CYP3A substrate. Concomitant use with a strong or moderate CYP3A inhibitor increases rilzabrutinib Cmax and AUC [see Clinical Pharmacology (12.3)], which increases the risk of WAYRILZ adverse reactions.

Strong and Moderate CYP3A Inducers

Avoid concomitant use of WAYRILZ with strong or moderate CYP3A inducers.

Rilzabrutinib is a CYP3A substrate. Concomitant use with a strong or moderate CYP3A inducer decreases rilzabrutinib Cmax and AUC [see Clinical Pharmacology (12.3)], which may reduce WAYRILZ efficacy.

Gastric Acid Reducing Agents

Administer the dose of WAYRILZ at least 2 hours before administration of an antacid or histamine H2 receptor antagonist. Avoid concomitant use of proton pump inhibitors with WAYRILZ.

Rilzabrutinib exhibits pH-dependent solubility. Acid reducing agents decrease rilzabrutinib exposure [see Clinical Pharmacology (12.3)], which may reduce WAYRILZ efficacy.

7.2 Effect of WAYRILZ on Other Drugs

CYP3A Substrates

Monitor for adverse reactions of the concurrently administered CYP3A substrate more frequently and consider dosage adjustment in accordance with the Prescribing Information of the CYP3A substrate.

Rilzabrutinib is a moderate inhibitor of CYP3A and increases exposure of these substrates [see Clinical Pharmacology (12.3)], which increases the risk of adverse reactions related to these substrates.

P-gp, BCRP, and OATP1B Substrates

Monitor for adverse reactions of the concurrently administered P-gp, BCRP, or OATP1B substrate more frequently, unless otherwise recommended in the substrate Prescribing Information, when WAYRILZ is used concomitantly with P-gp, BCRP, or OATP1B substrates where minimal substrate concentration changes may lead to serious adverse reactions.

Rilzabrutinib is an inhibitor of P-gp, BCRP and OATP1B in vitro. The effect of concomitant use of WAYRILZ with OATP1B and BCRP substrates has not been established in clinical studies. However, based on in vitro inhibitory potential [see Clinical Pharmacology (12.3)], concomitant use of WAYRILZ may increase the risk of adverse reactions related to these substrates.

8 USE IN SPECIFIC POPULATIONS

8.1 Pregnancy

Risk Summary

Based on animal data, WAYRILZ may cause fetal harm when administered to a pregnant woman. In animal reproduction studies, oral administration of rilzabrutinib to pregnant rats and rabbits during organogenesis at exposures 4- to 10-times the human exposure (based on AUC) at the maximum recommended human dose (MRHD) of 400 mg twice daily did not cause adverse developmental effects. However, adverse visceral and skeletal findings occurred in rat fetuses at a maternally toxic dose at exposures 22-times the human exposure (based on AUC) at the MRHD (see Data). There are no available clinical data on the use of WAYRILZ during pregnancy to evaluate for a drug-associated risk of major birth defects, miscarriage, or other adverse maternal or fetal outcomes. Advise pregnant women of the potential risk to a fetus.

The background risk of major birth defects and miscarriage for the indicated population is unknown. All pregnancies have a background risk of birth defects, loss, and other adverse outcomes. In the U.S. general population, the estimated background risk of major birth defects and miscarriage in clinically recognized pregnancies is 2% to 4% and 15% to 20%, respectively.

Data

Animal Data

Rilzabrutinib given to pregnant rats by oral gavage at 50, 150 or 300 mg/kg/day during the period of organogenesis (gestation day 7 to 17) did not cause adverse effects on embryo-fetal development at exposures approximately 10-times the clinical exposure at the maximum recommended human dose (MRHD), based on AUC. Increased incidence of post-implantation loss (25%), delayed ossification associated with a markedly lower (24%) mean fetal weight, and increased skeletal (scoliosis) and visceral malformations (abnormalities of major vessels, urogenital tract, and kidney) occurred in a preliminary study in rats at a maternally toxic dose of 500 mg/kg/day that resulted in exposures 22-times the clinical exposure at the MRHD, based on AUC.

Rilzabrutinib given to pregnant rabbits by oral gavage at 10, 30 or 100 mg/kg/day during the period of organogenesis (gestation day 7 to 19) did not cause adverse effects on embryo-fetal development at exposures approximately 4-times the clinical exposures at the MRHD, based on AUC. Renal visceral malformations occurred in a single fetus in a preliminary study in rabbits at 150 mg/kg/day that resulted in exposures 5.6-times the clinical exposure at the MRHD, based on AUC.

In a pre- and postnatal developmental toxicity study, pregnant rats were given rilzabrutinib by oral gavage at doses of 50, 150 or 300 mg/kg/day during the periods of gestation, parturition, and lactation (gestation day 7 to lactation day 21). Decreased body weight was observed in pups in the presence of maternal toxicity at 300 mg/kg/day, at exposures approximately 18-times the MRHD based on AUC. There were no effects of rilzabrutinib on the ability of F1 offspring to reproduce or on subsequent F2 development at any dose.

8.2 Lactation

Risk Summary

There are no data on the presence of rilzabrutinib or its metabolites in either human or animal milk, the effects on the breastfed child, or the effects on milk production. Due to the potential for adverse reactions in a breastfed child from WAYRILZ, advise lactating women not to breastfeed while taking WAYRILZ and for at least 1 week after the final dose.

8.3 Females and Males of Reproductive Potential

Based on preliminary animal data, WAYRILZ may cause fetal harm when administered to pregnant women [see Use in Specific Populations (8.1)].

Pregnancy Testing

Verify pregnancy status of females of reproductive potential prior to initiating WAYRILZ treatment.

Contraception

Females

Advise female patients of reproductive potential to use effective contraception during WAYRILZ treatment and for 1 week after stopping treatment.

8.4 Pediatric Use

Safety and effectiveness of WAYRILZ have not been established in pediatric patients.

8.5 Geriatric Use

Of the 202 patients in the LUNA-3 study [see Clinical Studies (14)], 36 (18%) patients were 65 years of age and older, and 9 (5%) patients were 75 years of age and older. No overall differences in safety and efficacy were observed between patients 65 years of age and older and younger adult patients.

8.6 Hepatic Impairment

Avoid administration of WAYRILZ in patients with moderate or severe hepatic impairment (Child-Pugh class B-C) because of potential for increased rilzabrutinib exposures. Dose modification is not required for patients with mild hepatic impairment (Child-Pugh class A) [see Clinical Pharmacology (12.3)].

8.7 Renal Impairment

Avoid use in patients with severe renal impairment. Patients with severe renal impairment were not studied. Dose modification is not required for patients with mild or moderate renal impairment [see Clinical Pharmacology (12.3)].

10 OVERDOSAGE

In the event of overdosage, closely monitor the patient for any signs or symptoms of adverse reactions and institute appropriate symptomatic treatment immediately.

Consider contacting the Poison Help line (1-800-222-1222) or a medical toxicologist for additional overdose management recommendations.

11 DESCRIPTION

WAYRILZ (rilzabrutinib) is a kinase inhibitor. Rilzabrutinib is a white to off-white solid, which is freely soluble in ethanol, sparingly soluble in isopropyl alcohol and practically insoluble in water.

The chemical name for rilzabrutinib is 1-Piperidinepropanenitrile, 3-[4-amino-3-(2-fluoro-4-phenoxyphenyl)-1H-pyrazolo[3,4-d]pyrimidin-1-yl]-α-[2-methyl-2-[4-(3-oxetanyl)-1-piperazinyl]propylidene]-β-oxo-, (3R)-. The molecular formula is C36H40FN9O3 and the molecular weight is 665.77 Daltons. The chemical structural formula of rilzabrutinib is shown below:

Each WAYRILZ film-coated tablet for oral administration contains 400 mg rilzabrutinib. The inactive ingredients in the tablet core are crospovidone (Type A), microcrystalline cellulose, and sodium stearyl fumarate. The inactive ingredients in the tablet coating are FD&C yellow #6/Sunset yellow FCF aluminum lake, macrogol/polyethylene glycol (PEG), polyvinyl alcohol partially hydrolyzed, talc, and titanium dioxide.

12 CLINICAL PHARMACOLOGY

12.1 Mechanism of Action

Rilzabrutinib is a small-molecule, covalent, reversible kinase inhibitor targeting Bruton's tyrosine kinase (BTK). Rilzabrutinib mediates its therapeutic effect in ITP through immune modulation including 1) inhibition of B cell activation, and 2) interruption of antibody-coated cell phagocytosis by Fcγ receptor (FcγR) in spleen and liver. In vitro, rilzabrutinib reduced autoantibody signaling mediated through the FcγR pathway, blocked B cell signaling, and decreased autoantibody generation through effects on B cell activation.

12.2 Pharmacodynamics

Plasma Exposure and BTK Occupancy

WAYRILZ has a short duration of systemic exposure with a long duration of action on the target due to its slow dissociation from BTK. At therapeutic doses in healthy participants, durable BTK occupancy in peripheral blood mononuclear cells was observed over a 24-hour period.

Cardiac Electrophysiology

In a Thorough QT study, concentration dependent shortening in the QTc interval was observed. Following a single dose of rilzabrutinib 400 mg, the mean maximum QTcF decrease of -7 msec (90% confidence interval: -9 msec to -5 msec) was observed at 2 hours post-dose. The mean maximum QTcF decrease at exposures 4-fold the highest recommended dose, i.e., 400 mg BID, was -10 msec (90% confidence interval: -12 msec to -8 msec) at 2 hours post-dose.

12.3 Pharmacokinetics

The pharmacokinetics of rilzabrutinib are presented as geometric mean (% coefficient of variation) unless otherwise specified. The Cmax and AUC of rilzabrutinib increase proportionally following administration of multiple doses of 300 mg to 600 mg. Steady-state plasma levels are reached within 3 days with accumulation up to 1.3-fold at the approved recommended dosage. Following daily doses of 400 mg rilzabrutinib twice daily, the steady-state Cmax and AUC24h are 150 ng/mL (56%) and 1540 ng.h/mL (57.5%), respectively.

Absorption

The absolute oral bioavailability of rilzabrutinib is 4.7%. Following a single oral dose of 400 mg rilzabrutinib, the median time to peak plasma concentration (Tmax) is approximately 2 hours.

Effect of Food:

Rilzabrutinib AUC and Cmax decreased by 20% and 31%, respectively, following administration of a single oral 400 mg dose with a high fat meal (approximately 1,000 calories with 50% of total caloric content from fat).

Distribution

The volume of distribution at terminal phase (Vz) after IV administration is 149L. Rilzabrutinib is 97.5% bound to plasma proteins and the blood-to-plasma ratio is 0.786.

Metabolism

Rilzabrutinib is predominantly metabolized by cytochrome P450 3A.

Elimination

The clearance of rilzabrutinib is time-independent. Following multiple doses of 400 mg twice daily rilzabrutinib in patients with ITP, mean CL/F ranged from 246 to 911 L/h. Based on the population pharmacokinetic analysis in patients with ITP, the mean CL/F was 516 L/h.

In Phase 1 studies, the half-life of rilzabrutinib ranged between 1.6 to 4.5 hours.

Excretion

Following administration of a single 400 mg 14C-labeled rilzabrutinib dose in healthy subjects, approximately 86% of the dose was recovered in feces (9% unchanged) and to a lesser extent in urine (~5%) and bile (~6%). Approximately 0.03% of rilzabrutinib was excreted unchanged in the urine.

Special Populations

No clinically significant differences in the pharmacokinetics of rilzabrutinib were observed based on age (12 to 80 years), sex, race, mild to moderate renal impairment (CLCR 46 to 89 mL/min), or mild hepatic impairment (Child-Pugh class A). Rilzabrutinib exposure (both Cmax and AUC) increased by approximately 4.5-fold in participants with moderate hepatic impairment (Child-Pugh class B). Patients with severe hepatic impairment (Child-Pugh class C) and CLCR <46 mL/min have not been studied.

Drug Interaction Studies

Clinical Studies and Model-Informed Approaches

Effect of Other Drugs on Rilzabrutinib

Strong CYP3A inhibitors: Concomitant use with ritonavir (strong CYP3A inhibitor) increased rilzabrutinib Cmax by approximately 5-fold and AUC by 8-fold at steady state.

Moderate CYP3A inhibitors: Concomitant use with moderate CYP3A inhibitors (fluconazole, erythromycin and verapamil) is predicted to increase rilzabrutinib Cmax and AUC by approximately 3-fold at steady state.

Weak CYP3A inhibitors: Cimetidine is predicted to increase rilzabrutinib Cmax by approximately 2-fold and AUC by 1.6-fold.

Strong CYP3A inducers: Coadministration of rifampin (strong CYP3A inducer) decreased rilzabrutinib Cmax and AUC by approximately 80% at steady state.

Moderate CYP3A inducers: Coadministration of moderate CYP3A inducers (efavirenz, rifabutin) is predicted to reduce rilzabrutinib Cmax and AUC by up to 70% at steady state.

Weak CYP3A inducers: Modafinil is predicted to reduce rilzabrutinib Cmax and AUC by 20%.

Proton pump inhibitor: Coadministration of esomeprazole (proton pump inhibitor) decreased rilzabrutinib Cmax by 55% and AUC by 51%.

H2 receptor antagonist: Administration of famotidine (H2 receptor antagonist) two hours after the evening dose of rilzabrutinib decreased the next morning dose of rilzabrutinib Cmax by 35% and AUC by 28%.

P-glycoprotein (P-gp) inhibitor: Coadministration of quinidine (P-gp inhibitor) increased rilzabrutinib Cmax and AUC by approximately 13% at steady state.

Effect of Rilzabrutinib on Other Drugs

CYP3A4 substrates: Concomitant use of a single dose of rilzabrutinib 400 mg with midazolam (sensitive CYP3A inhibitor) increased midazolam Cmax and AUC by 2.2-fold as observed in study with healthy participants. Midazolam AUC is predicted to increase up to 3.0-fold in patients with immune thrombocytopenia following coadministration with 400 mg rilzabrutinib twice daily.

In Vitro Studies

CYP Enzymes: Rilzabrutinib is a substrate of CYP3A. Rilzabrutinib is both an inhibitor and inducer of CYP3A.

Transporters: Rilzabrutinib is a substrate of P-gp and BCRP, but not a substrate for OAT1, OAT3, OCT1, OCT2, OATP1B1, OATP1B3, or BSEP. Rilzabrutinib inhibits P-gp, BCRP, OATP1B1, OATP1B3, and BSEP at clinically relevant concentrations.

13 NONCLINICAL TOXICOLOGY

Carcinogenesis, Mutagenesis, Impairment of Fertility

Rilzabrutinib was not carcinogenic in a 6-month study in Tg.rasH2 mice at doses up to 300 mg/kg/day. In a 2-year rat carcinogenicity study at doses of 10, 30 or 100 and 5, 15 or 50 mg/kg/day in males and females, respectively, there were no rilzabrutinib-related tumors. The non-carcinogenic dose was the highest dose tested of 100 mg/kg/day for males and 50 mg/kg/day for females.

Rilzabrutinib was not mutagenic in an in vitro bacterial reverse mutagenicity (Ames) assay, was not clastogenic in an in vitro human peripheral lymphocyte chromosomal aberration assay, nor was it clastogenic in an in vivo bone marrow micronucleus assay in rats.

In a fertility study in male and female rats, rilzabrutinib was administered for a minimum of 28 days (males) and 15 days (females) prior to cohabitation and continued through gestation day 7 at doses of 50, 150 or 300 mg/kg/day by oral gavage. Rilzabrutinib had no effect on mating, estrous cycle, fertility, sperm parameters, or any ovarian and uterine parameters at any dose.

14 CLINICAL STUDIES

Immune Thrombocytopenia (ITP)

The safety and efficacy of WAYRILZ in adult patients with primary persistent or chronic ITP was evaluated in a randomized, double-blind (DB), placebo-controlled, parallel-group study consisting of 24 weeks of blinded treatment followed by an open-label (OL) period [LUNA-3 Study (NCT04562766)]. Patients received an initial 12 weeks of DB period treatment. Those who achieved platelet count response at 12 weeks were eligible to continue the full 24-week DB period. The patients enrolled in this study had an unsustained response to either intravenous immunoglobulin (IVIg/anti-D) or corticosteroid (CS) or had a documented intolerance or insufficient response to any appropriate course of standard-of-care ITP therapy.

Patients were randomized 2:1 to receive WAYRILZ 400 mg or placebo twice daily and randomization was stratified based on prior splenectomy (yes/no) and severity of thrombocytopenia (platelet count <15 ×10^9/L or ≥15 ×10^9/L).

Concomitant ITP medicines [oral CS and/or thrombopoietin receptor agonist (TPO-RA)] were allowed at stable doses at least 2 weeks before the start of the study and throughout the DB period.

In the LUNA-3 Study, 202 patients were randomized and treated, 133 to the WAYRILZ group and 69 to the placebo group. At baseline, the median age was 47 years (range: 18 to 80 years), 63% were female, 62% were Caucasian, 32% Asian, 1% were Black or African American, 2% were American Indian or Alaska native, 20% were Hispanic or Latino/a, and 77% were not Hispanic or Latino/a. Baseline demographics were generally similar across groups with the exception of sex which was 59% female in the WAYRILZ group and 71% in the placebo group.

At baseline 93% of patients had chronic ITP (i.e., for 1 year or longer), with a median time since ITP diagnosis of 7.69 years (range: 0.3, 52.2), and 28% had undergone splenectomy. The median platelet count was 15.3 × 10^9/L, with almost half (48%) less than 15 × 10^9/L. The median number of prior therapies, including splenectomy, was 4 (range: 1, 15). Prior ITP treatments varied, with the most common prior therapies being CS (96%), TPO-RAs (69%), IVIg or anti-D immunoglobulins (55%), and anti-CD20 monoclonal antibody/rituximab (35%). In addition, at baseline 66% of patients received both CS and TPO-RAs. Baseline disease characteristics were generally similar across both groups.

During the DB period, the median duration of exposure was 98 days (range: 22 to 182) and 84 days (range: 17 to 173) for the WAYRILZ group and placebo group, respectively. The cumulative duration of treatment exposure was 44 participant-years and 18 participant-years for the WAYRILZ and placebo groups, respectively. Concomitant use of CS and/or TPO-RA with study drug occurred in 60% and 67% of patients in the WAYRILZ and placebo arms, respectively.

During the first 12 weeks of the DB period, 85 (63.9%) patients and 22 (31.9%) patients in the WAYRILZ group and placebo group, respectively, achieved platelet count response (≥50 × 10^9/L or between 30 × 10^9/L and <50 × 10^9/L and doubled from baseline). Those who achieved platelet count response were eligible to continue the DB period.

The efficacy of WAYRILZ was based on durable platelet response. A durable platelet response was defined as a weekly platelet count ≥50 × 10^9/L for ≥ two-thirds of at least 8 non-missing weekly scheduled platelet measurements during the last 12 weeks of the 24-week DB period in the absence of rescue therapy, provided that at least 2 non-missing weekly scheduled platelet measurements were ≥50 × 10^9/L during the last 6 weeks of the DB period.

The results of the major efficacy endpoints during the DB period are summarized in Table 2.

Table 2: LUNA-3 Study Outcomes During the 24-week DB Period – Adult Population
Study Outcomes | Statistic | WAYRILZ 400 mg BID (N=133) | Placebo (N=69)
Durable Platelet Response [p-value was derived by Cochran-Mantel-Haenszel (CMH) test adjusted by stratification factors.] | n (%) | 31 (23.3) | 0 (0)
Durable Platelet Response [p-value was derived by Cochran-Mantel-Haenszel (CMH) test adjusted by stratification factors.] | 95% CI | 16.12, 30.49 | 0.00, 0.00
Durable Platelet Response [p-value was derived by Cochran-Mantel-Haenszel (CMH) test adjusted by stratification factors.] | Risk difference (95% CI) vs placebo | 23.1 (15.95, 30.31)
Durable Platelet Response [p-value was derived by Cochran-Mantel-Haenszel (CMH) test adjusted by stratification factors.] | p-value | <0.0001
Number of Weeks with Platelet Response [Numbers of weeks with platelet response was based on 24-week blinded treatment period. Platelet counts assessed within 4 weeks of rescue medication intake are considered as no response; missing weekly platelet counts due to any reasons are considered as no response. p-value was derived by a mixed-effect model with repeated measures on longitudinal binary data with treatment, stratification factors, week (Weeks 2 to 25), treatment-by-week interaction as categorical fix effects.]
≥50 × 10^9/L or between 30 × 10^9/L and <50 × 10^9/L and doubled from baseline | LS Mean (SE) | 7.18 (0.75) | 0.72 (0.35)
≥50 × 10^9/L or between 30 × 10^9/L and <50 × 10^9/L and doubled from baseline | LS Mean difference (SE) vs placebo | 6.46 (0.78)
≥50 × 10^9/L or between 30 × 10^9/L and <50 × 10^9/L and doubled from baseline | 95% CI | 4.92, 7.99
≥50 × 10^9/L or between 30 × 10^9/L and <50 × 10^9/L and doubled from baseline | p-value | <0.0001
≥30 × 10^9/L and doubled from baseline | LS Mean (SE) | 6.95 (0.75) | 0.64 (0.34)
≥30 × 10^9/L and doubled from baseline | LS Mean difference (SE) vs placebo | 6.31 (0.78)
≥30 × 10^9/L and doubled from baseline | 95% CI | 4.79, 7.83
≥30 × 10^9/L and doubled from baseline | p-value | <0.0001
Time to First Platelet Response [Platelet count ≥50 × 10^9/L or between 30 × 10^9/L and <50 × 10^9/L and at least doubled from baseline in absence of rescue therapy; p-value was derived by log-rank test adjusted by stratification factors.] | Median number of days to first platelet count (95% CI) | 36 (22, 44) | NR
Time to First Platelet Response [Platelet count ≥50 × 10^9/L or between 30 × 10^9/L and <50 × 10^9/L and at least doubled from baseline in absence of rescue therapy; p-value was derived by log-rank test adjusted by stratification factors.] | Hazard ratio (95% CI) vs placebo | 3.10 (1.95, 4.93)
Time to First Platelet Response [Platelet count ≥50 × 10^9/L or between 30 × 10^9/L and <50 × 10^9/L and at least doubled from baseline in absence of rescue therapy; p-value was derived by log-rank test adjusted by stratification factors.] | p-value | <0.0001
Time to First Platelet Response [Platelet count ≥50 × 10^9/L or between 30 × 10^9/L and <50 × 10^9/L and at least doubled from baseline in absence of rescue therapy; p-value was derived by log-rank test adjusted by stratification factors.] | Abbreviations: LS=Least Square; NR=Not Reached; CI=Confidence Interval; SE=Standard Error.

Rescue medication was required by 33% and 58% of patients receiving WAYRILZ and placebo, respectively. The median time to first use of rescue therapy was not reached in the WAYRILZ group and 56 days in the placebo group.

During the OL period, 7/73 (10%) patients who received WAYRILZ during the DB period achieved a durable response for the first time.

16 HOW SUPPLIED/STORAGE AND HANDLING

The 400 mg WAYRILZ film-coated tablets are orange, capsule-shaped, and debossed with "P" on one side and "400" on the other side.

How Supplied:

Package Size/Type | Content | NDC Number
60-count bottle | Bottle containing 60 film-coated tablets with a child-resistant closure | 58468-0251-6
56-count carton | Carton containing 2 blister packs. Each blister pack (58468-0251-0) contains 28 film-coated tablets. | 58468-0251-5

Storage

Store at room temperature between 20°C to 25°C (68°F to 77°F); excursions are permitted between 15°C to 30°C (59°F to 86°F) [see USP Controlled Room Temperature]. Store and dispense in the original package. Protect from light and moisture.

17 PATIENT COUNSELING INFORMATION

Advise the patient to read the FDA-approved patient labeling (Patient Information).

Storage Instructions

Instruct patients to store WAYRILZ at room temperature in the original package and to protect from light and moisture.

Administration Instructions

Instruct patients to take WAYRILZ orally twice daily at approximately the same time each day with or without food. Advise patients that WAYRILZ tablets should be swallowed whole with a glass of water, and not to cut, crush or chew the tablets [see Dosage and Administration (2.2)].

Missed Dose

Advise patients that if they miss a dose of WAYRILZ, they should take it as soon as possible on the same day and at least 2 hours apart from the next regular scheduled dose.

Drug Interactions

Advise patients to inform their healthcare providers of all concomitant medications, including over-the-counter medications, vitamins, and herbal supplements. Advise patients to avoid eating grapefruit, starfruit, and Seville oranges and products containing these fruits with WAYRILZ [see Drug Interactions (7.1, 7.2)].

Serious Infections

Advise patients of the possibility of serious infection, and to report any signs or symptoms [see Warnings and Precautions (5.1)].

Hepatotoxicity, Including Drug-Induced Liver Injury

Inform patients that liver problems, including severe, life-threatening, or fatal hepatitis, DILI and abnormalities in liver tests, have occurred in patients treated with BTK inhibitors. Advise patients to contact their healthcare provider immediately if they experience abdominal discomfort, dark urine, or jaundice [see Warnings and Precautions (5.2)].

Embryo-Fetal Toxicity

Advise female patients of reproductive potential that WAYRILZ may cause fetal harm and to inform their healthcare providers of a known or suspected pregnancy. Advise females of reproductive potential to use effective contraception during treatment with WAYRILZ and for 1 week after the last dose [see Warnings and Precautions (5.3), Use in Specific Populations (8.1, 8.3)].

Lactation

Advise women not to breastfeed during treatment with WAYRILZ and for at least 1 week after the final dose [see Use in Specific Populations (8.2)].

Manufactured for:
Genzyme Corporation
Cambridge, MA 02141
A SANOFI COMPANY © 2025 Sanofi. All rights reserved.

For patent information: https://www.sanofi.us/en/products-and-resources/patents

WAYRILZ is a trademark of Sanofi or an affiliate.

PATIENT INFORMATION
WAYRILZ™ (WAY-rilz)
(rilzabrutinib)
tablets, for oral use

What is WAYRILZ?
WAYRILZ is a prescription medicine that is used to treat adults with persistent or chronic immune thrombocytopenia (ITP) who have received a prior treatment that did not work well enough.
It is not known if WAYRILZ is safe and effective in children.

Before taking WAYRILZ, tell your healthcare provider about all of your medical conditions, including if you:

- have liver problems
- have kidney problems
- are pregnant or plan to become pregnant. WAYRILZ may harm your unborn baby. If you are able to have a baby, your healthcare provider will do a pregnancy test before starting treatment with WAYRILZ.
  - Females who are able to become pregnant should use effective birth control (contraception) during treatment with WAYRILZ and for 1 week after the last dose.
- are breastfeeding or plan to breastfeed. It is not known if WAYRILZ passes into your breast milk. Do not breastfeed during treatment with WAYRILZ and for at least 1 week after the last dose.

Tell your healthcare provider about all the medicines you take, including prescription and over‑the‑counter medicines, vitamins, and herbal supplements. Taking WAYRILZ with certain other medicines may affect how WAYRILZ works and can cause side effects. WAYRILZ may also affect how other medicines work. Know the medicines you take. Keep a list of them and show it to your healthcare provider and pharmacist when you get a new medicine.

How should I take WAYRILZ?

- Take WAYRILZ exactly as your healthcare provider tells you to take it.
- Do not change your dose or stop taking WAYRILZ unless your healthcare provider tells you to.
- Take WAYRILZ 2 times a day at about the same time each day.
- Take WAYRILZ with or without food.
- Swallow WAYRILZ tablets whole with a glass of water. Do not cut, crush, or chew the tablets.
- If you experience diarrhea, nausea, or stomach area (abdominal) pain during treatment with WAYRILZ, taking it with food may reduce these side effects.
- If you take an antacid or H2 blocker medicine, take your dose of WAYRILZ at least 2 hours before taking an antacid or H2 blocker medicine. If you take a Proton Pump Inhibitor (PPI) medicine, talk to your healthcare provider.
- If you miss a dose of WAYRILZ, take the missed dose as soon as you remember on the same day and at least 2 hours apart from the next regular scheduled dose.
- If you take too much WAYRILZ, call your healthcare provider or Poison Help Line at 1-800-222-1222.

What should I avoid while taking WAYRILZ?

- You should avoid grapefruit, starfruit and products that have these fruits, and Seville oranges (often used in marmalades) during treatment with WAYRILZ. These products may increase the amount of WAYRILZ in your blood, which increases the risk of side effects of WAYRILZ.

What are the possible side effects of WAYRILZ?
WAYRILZ may cause serious side effects, including:

- Serious infections. WAYRILZ can increase the risk of infections, including serious infections that can lead to death. Your healthcare provider will check you for signs and symptoms of infection during your treatment with WAYRILZ. Tell your healthcare provider right away if you get any signs or symptoms of infection, including fever, chills, or flu-like symptoms.
- Liver problems including Drug-Induced Liver Injury (DILI). Liver problems, which may be severe, life-threatening, or lead to death have happened in people treated with Bruton’s tyrosine kinase (BTK) inhibitors. Your healthcare provider will do blood tests to check your liver before and as necessary during treatment with WAYRILZ. Tell your healthcare provider right away if you have any signs or symptoms of liver problems, including stomach-area (abdominal) pain or discomfort, dark or “tea-colored” urine, or yellowing of the skin or the white part of your eyes.

The most common side effects of WAYRILZ include:

- diarrhea
- nausea
- headache
- stomach area (abdominal) pain
- COVID-19

These are not all of the possible side effects of WAYRILZ.
Call your doctor for medical advice about side effects. You may report side effects to FDA at 1-800-FDA-1088.

How should I store WAYRILZ?

- Store WAYRILZ at room temperature between 20°C to 25°C (68°F to 77°F).
- Store WAYRILZ tablets in the original packaging.
- Protect WAYRILZ from light and moisture.

Keep WAYRILZ and all medicines out of the reach of children.

General information about the safe and effective use of WAYRILZ.
Medicines are sometimes prescribed for purposes other than those listed in a Patient Information leaflet. Do not use WAYRILZ for a condition for which it was not prescribed. Do not give WAYRILZ to other people, even if they have the same symptoms that you have. It may harm them. You can ask your pharmacist or healthcare provider for information about WAYRILZ that is written for health professionals.

What are the ingredients in WAYRILZ?
Active ingredients: rilzabrutinib
Inactive ingredients: Tablet core: crospovidone (Type A), microcrystalline cellulose, and sodium stearyl fumarate; Tablet coating: FD&C yellow #6/Sunset yellow FCF aluminum lake, macrogol/polyethylene glycol (PEG), polyvinyl alcohol partially hydrolyzed, talc, and titanium dioxide.

Manufactured for:
Genzyme Corporation
Cambridge, MA 02141
A SANOFI COMPANY
WAYRILZ is a trademark of Sanofi or an affiliate.
For more information go to www.wayrilz.com or call 1-833-723-5463.

This Patient Information has been approved by the U.S. Food and Drug Administration.

Issued: 08/2025

PRINCIPAL DISPLAY PANEL - 60 Tablet Bottle Carton

NDC 58468-0251-6
Rx only

WAYRILZ™
(rilzabrutinib) tablets
400 mg

60 tablets
sanofi

PRINCIPAL DISPLAY PANEL - 28 Tablet Blister Pack

NDC 58468-0251-0
Rx only

Press and
hold here
1

WAYRILZ™
(rilzabrutinib) tablets
400 mg per tablet

2
Pull out
blister card

Each blister pack contains 28 tablets.

sanofi

PRINCIPAL DISPLAY PANEL - 56 Tablet Blister Pack Carton

NDC 58468-0251-5
Rx only

WAYRILZ™
(rilzabrutinib) tablets
400 mg per tablet

Each carton contains a total of 56 tablets
in two blister packs of 28 tablets each.

sanofi